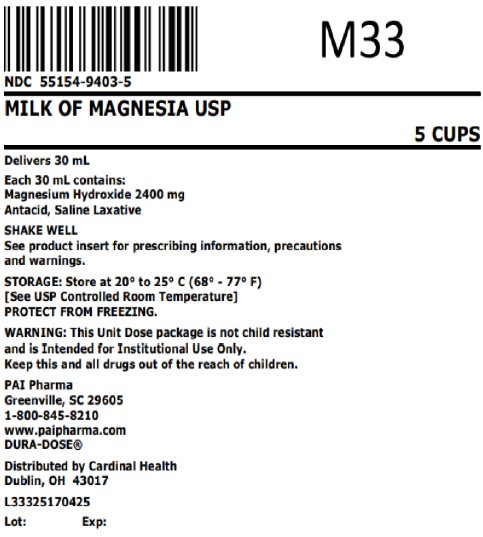 DRUG LABEL: Milk of Magnesia
NDC: 55154-9403 | Form: SUSPENSION
Manufacturer: Cardinal Health 107, LLC
Category: otc | Type: HUMAN OTC DRUG LABEL
Date: 20250422

ACTIVE INGREDIENTS: MAGNESIUM HYDROXIDE 400 mg/5 mL
INACTIVE INGREDIENTS: HYPROMELLOSE 2910 (4000 MPA.S); METHYLPARABEN; POTASSIUM CITRATE; PROPYLENE GLYCOL; PROPYLPARABEN; WATER; CYCLOMETHICONE 4; SACCHARIN SODIUM; SORBITOL

Milk of Magnesia

Drug Facts

Active ingredient (in each 5 mL)

Magnesium hydroxide 400 mg

Purpose

Saline laxative

Uses

As an Antacid

- heartburn
- upset/sour stomach
- acid indigestion

As a Laxative (usually within ½ to 6 hours)

- occasional constipation (irregularity)

Warnings

Ask a doctor before use if you have

- kidney disease
- a magnesium-restricted diet
- stomach pain, nausea, or vomiting
- a sudden change in bowel habits that lasts over 14 days

Ask a doctor or pharmacist before use If you are taking a prescription drug. This product may interact with certain prescription drugs.

Stop use and ask a doctor if

- you have rectal bleeding or no bowel movement after using this product. These could be signs of a serious condition.
- you need to use a laxative for more than 1 week

PREGNANCY OR BREAST FEEDING

If pregnant or breast-feeding, ask a health professional before use.

Keep out of reach of children. In case of overdose, get medical help or contact a Poison Control Center right away.

Directions

As an Antacid

- do not exceed the maximum recommended daily dose in a 24 hour period
- shake well before use
- can be taken with water
- mL = milliliter

adults and children 12 years of age and over | 5 to 15 mL (1 to 3 teaspoonfuls)
children under 12 years of age | ask a doctor

As a Laxative

- do not exceed the maximum recommended daily dose of 60 mL in a 24 hour period
- shake well before use
- dose may be taken once a day preferably at bedtime, in divided doses, or as directed by a doctor. Drink a full glass (8 oz) of liquid with each dose.
- mL = milliliter; TBSP = Tablespoon

adults and children 12 years and older | 30 mL (2 TBSP) to 60 mL (4 TBSP)
children 6 – 11 years | 15 mL (1 TBSP) to 30 mL (2 TBSP)
children under 6 years | ask a doctor

Other information

- each teaspoonful (5 mL) contains:magnesium 400 mg
- store at room temperature, 20° - 25°C (68° - 77°F). Avoid freezing.
- Milk of Magnesia USP (white suspension, spearmint flavor) is supplied in the following oral dosage form:

Overbagged with 5 x 30 mL unit dose cups in each bag, NDC 55154-9403-5

See product insert for prescribing information, precautions and warnings.

PROTECT FROM FREEZING.

WARNING: This Unit Dose package is not child resistant and is Intended for Institutional Use Only. Keep this and all drugs out of the reach of children.

Inactive ingredients

flavoring, hydroxypropyl methylcellulose, methylparaben, potassium citrate, propylene glycol, propylparaben, purified water, antifoam af emulsion, sodium saccharin, and sorbitol.

Questions or comments?

Call 1-800-845-8210

MANUFACTURED BY
Pharmaceutical
Associates, Inc.
Greenville, SC 29605

www.paipharm.com

DURA-DOSE®

F0431300721

Distributed By:

Cardinal Health

Dublin, OH 43017

L33325170425

Principal Display Panel

NDC 55154-9403-5

MILK OF MAGNESIA USP

5 CUPS